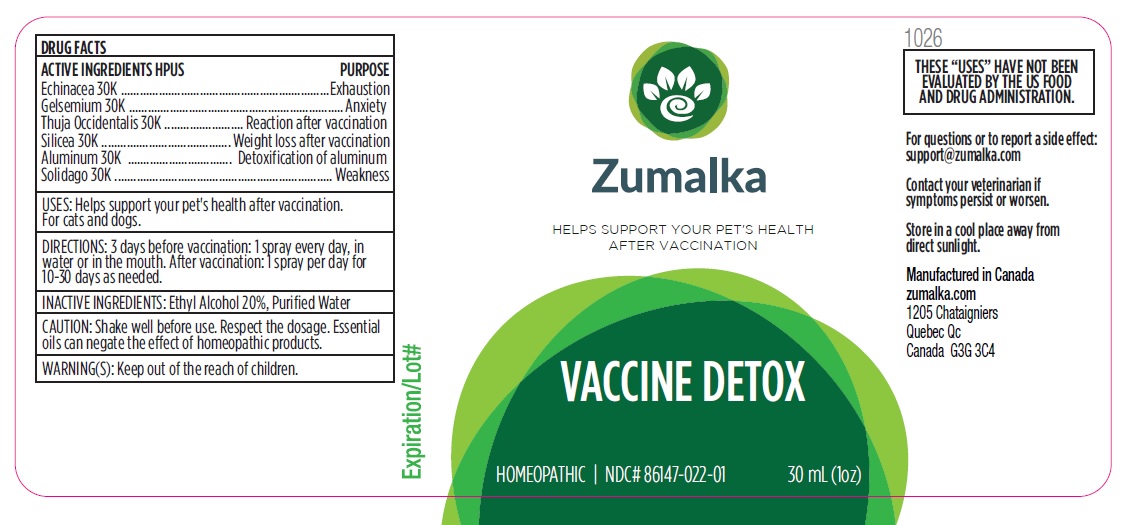 DRUG LABEL: VACCINE DETOX
NDC: 86147-022 | Form: LIQUID
Manufacturer: Groupe Cyrenne Inc.
Category: homeopathic | Type: OTC ANIMAL DRUG LABEL
Date: 20251120

ACTIVE INGREDIENTS: ECHINACEA, UNSPECIFIED 30 [kp_C]/30 mL; GELSEMIUM SEMPERVIRENS ROOT 30 [kp_C]/30 mL; THUJA OCCIDENTALIS LEAFY TWIG 30 [kp_C]/30 mL; SOLIDAGO VIRGAUREA FLOWERING TOP 30 [kp_C]/30 mL; SILICON DIOXIDE 30 [kp_C]/30 mL; ALUMINUM 30 [kp_C]/30 mL
INACTIVE INGREDIENTS: WATER; ALCOHOL

Active ingredient Purpose

Echinacea 30k, Exhaustion

Gelsemium 30k, Anxiety

Thuja Occidentalis 30k, Reaction after vaccination

Silicea 30k, Weight loss after vaccination

Solidago 30k, Weakness

Aluminum 30k Detoxification of aluminum

Uses

Helps support your pet's health after vaccination. For cats and dogs.

Warnings

Keep out of reach of children.

Direction

3 days before vaccination: 1 spray every day, in water or in the mouth.
After vaccination: 1 spray per day for 10-30 days as needed.

Inactive ingredient

Ethyl alcohol 20%, purified water

Cautions

Shake well before use. Respect the dosage. Essential oils can negate the effects of homeopathic products. Store in a cool place away from direct sunlight.